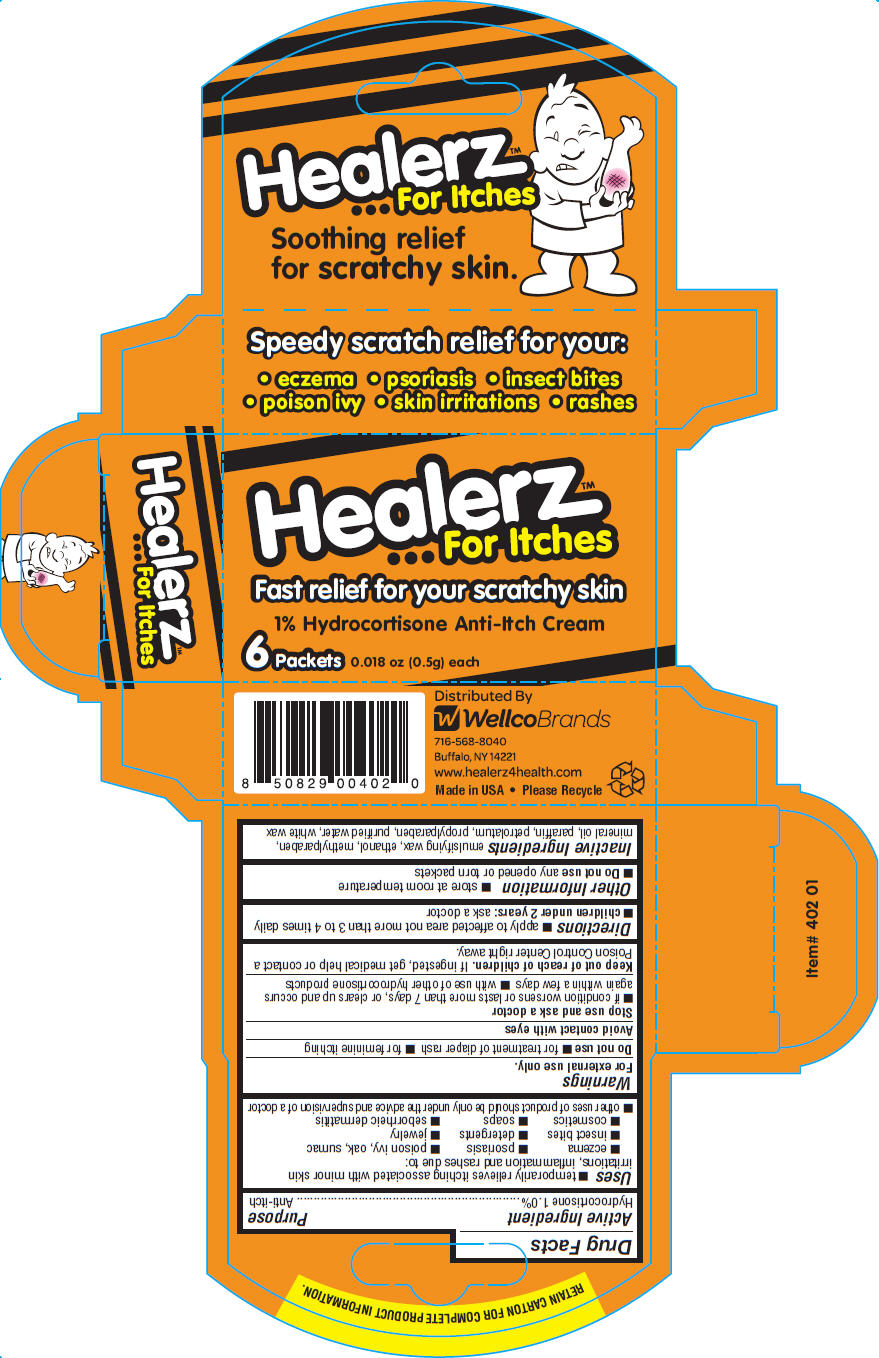 DRUG LABEL: Healerz for Itches
NDC: 50485-102 | Form: CREAM
Manufacturer: Wellco Brands LLC
Category: otc | Type: HUMAN OTC DRUG LABEL
Date: 20130109

ACTIVE INGREDIENTS: HYDROCORTISONE 1 g/100 g
INACTIVE INGREDIENTS: ALCOHOL; METHYLPARABEN; MINERAL OIL; PARAFFIN; PETROLATUM; PROPYLPARABEN; WATER; WHITE WAX

Healerz™ …for Itches

Drug Facts

Active Ingredient

Hydrocortisone 1.0%

Purpose

Anti-itch

Uses

- temporarily relieves itching associated with minor skin irritations, inflammation and rashes due to:
  - eczema
  - psoriasis
  - poison ivy, oak, sumac
  - insect bites
  - detergents
  - jewelry
  - cosmetics
  - soaps
  - seborrheic dermatitis
- other uses of product should be only under the advice and supervision of a doctor

Warnings

For external use only.

Do not use

- for treatment of diaper rash
- for feminine itching

WHEN USING

Avoid contact with eyes

Stop use and ask a doctor

- if condition worsens or lasts more than 7 days, or clears up and occurs again within a few days
- with use of other hydrocortisone products

Keep out of reach of children. If ingested, get medical help or contact a Poison Control Center right away.

Directions

- apply to affected area not more than 3 to 4 times daily
- children under 2 years: ask a doctor

Other Information

- store at room temperature
- Do not use any opened or torn packets

Inactive Ingredients

emulsifying wax, ethanol, methylparaben, mineral oil, paraffin, petrolatum, propylparaben, purified water, white wax

Distributed By
WellcoBrands
716-568-8040
Buffalo, NY 14221

PRINCIPAL DISPLAY PANEL - 6 Packet Carton

Healerz™
...For Itches

Fast relief for your scratchy skin

1% Hydrocortisone Anti-Itch Cream

6 Packets 0.018 oz (0.5g) each